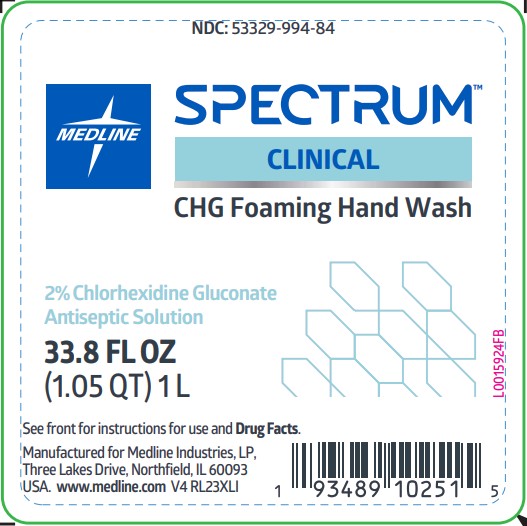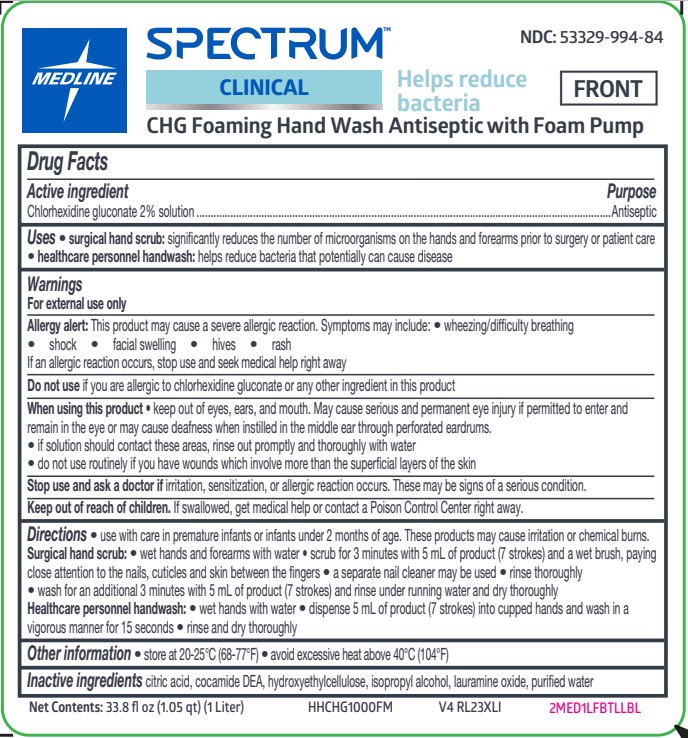 DRUG LABEL: foaming hand wash
NDC: 53329-994 | Form: LIQUID
Manufacturer: Medline Industries, LP
Category: otc | Type: HUMAN OTC DRUG LABEL
Date: 20250908

ACTIVE INGREDIENTS: CHLORHEXIDINE GLUCONATE 20 mg/1 mL
INACTIVE INGREDIENTS: COCO DIETHANOLAMIDE; LAURAMINE OXIDE; ISOPROPYL ALCOHOL; HYDROXYETHYL CELLULOSE (2000 CPS AT 1%); CITRIC ACID MONOHYDRATE; WATER

994 CHG Foaming Hand Wash

Active ingredient

Chlorhexidine gluconate 2% solution

Purpose

Antiseptic

Uses

- • surgical hand scrub: significantly reduces the number of microorganisms on the hands and forearms prior to surgery or patient care
- • healthcare personnel handwash: helps reduce bacteria that potentially can cause disease

Warnings

For external use only

Allergy alert: This product may cause a severe allergic reaction. Symptoms may include:

- • wheezing/difficulty breathing
- • shock
- • facial swelling
- • hives
- • rash

If an allergic reaction occurs, stop use and seek medical help right away

Do not use

if you are allergic to chlorhexidine gluconate or any other ingredient in this product

When using this product

- • keep out of eyes, ears, and mouth. May cause serious and permanent eye injury if permitted to enter and remain in the eye or may cause deafness when instilled in the middle ear through perforated eardrums.
- • if solution should contact these areas, rinse out promptly and thoroughly with water
- • do not use routinely if you have wounds which involve more than the superficial layers of the skin

Stop use and ask a doctor if

irritation, sensitization, or allergic reaction occurs. These may be signs of a serious condition.

Keep out of reach of children.

If swallowed, get medical help or contact a Poison Control Center right away.

Directions

- • use with care in premature infants or infants under 2 months of age. These products may cause irritation or chemical burns.

Surgical hand scrub:

- • wet hands and forearms with water
- • scrub for 3 minutes with 5 mL of product (7 strokes) and a wet brush, paying close attention to the nails, cuticles and skin between the fingers
- • a separate nail cleaner may be used
- • rinse thoroughly
- • wash for an additional 3 minutes with 5 mL of product (7 strokes) and rinse under running water and dry thoroughly

Healthcare personnel handwash:

- • wet hands with water
- • dispense 5 mL of product (7 strokes) into cupped hands and wash in a vigorous manner for 15 seconds
- • rinse and dry thoroughly

Other information

- • store at 20-25°C (68-77°F)
- • avoid excessive heat above 40°C (104°F)

Inactive ingredients

citric acid, cocamide DEA, hydroxyethylcellulose, isopropyl alcohol, lauramine oxide, purified water

Manufacturing Information

Manufactured for: Medline Industries, LP

Three Lakes Drive, Northfield, IL 60093 USA

Made in USA

www.medline.com

REF: HHCHG1000FM

V4 RL23XLI